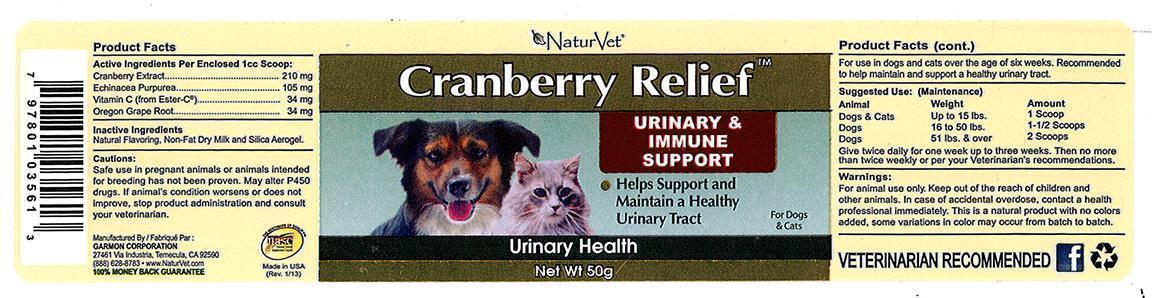 DRUG LABEL: Cranberry Relief
NDC: 27135-0356 | Form: POWDER
Manufacturer: The Garmon Corporation
Category: animal | Type: OTC ANIMAL DRUG LABEL
Date: 20131111

ACTIVE INGREDIENTS: CRANBERRY 210 mg/1 1; ECHINACEA PURPUREA 105 mg/1 1; CALCIUM ASCORBATE 34 mg/1 1; MAHONIA AQUIFOLIUM ROOT BARK 34 mg/1 1
INACTIVE INGREDIENTS: STEVIA LEAF; COW MILK; SILICON DIOXIDE

NaturVet Cranberry Relief

Active Ingredients Per enclosed 1cc scoop:
Cranberry Extract...........................210 mg
Echinacea Purpurea.......................105 mg
Vitamin C (from Ester-C)..................34 mg
Oregon Grape Root.........................34 mg

Inactive Ingredients
Natural Flavoring, Non-Fat Dry Milk and Silica Aerogel.

PRECAUTIONS

Cautions:
Safe use in pregnant animals or animals intended for breeding has not been proven. May alter P450 drugs. If animal’s condition worsens or does not improve, stop product administration and consult your veterinarian.

PURPOSE

For use in dogs and cats over the age of six weeks. Recommended to help maintain and support a healthy urinary tract.

DOSAGE AND ADMINISTRATION

Suggested Use: (Maintenance)
Animal Weight Amount
Dogs & Cats up to 15 lbs. 1 cc scoop
Dogs 16 to 50 lbs. 1-1/2 scoops
Dogs 51 + lbs. 2 scoops
Give twice daily for one week up to three weeks. Then no more than twice weekly or per your veterinarian’s recommendations.

Warnings:

For animal use only. Keep out of reach of children and other animals. In case of accidental overdose, contact health professional immediately. This is a natural product with no colors added, some variations in color may occur from batch to batch.